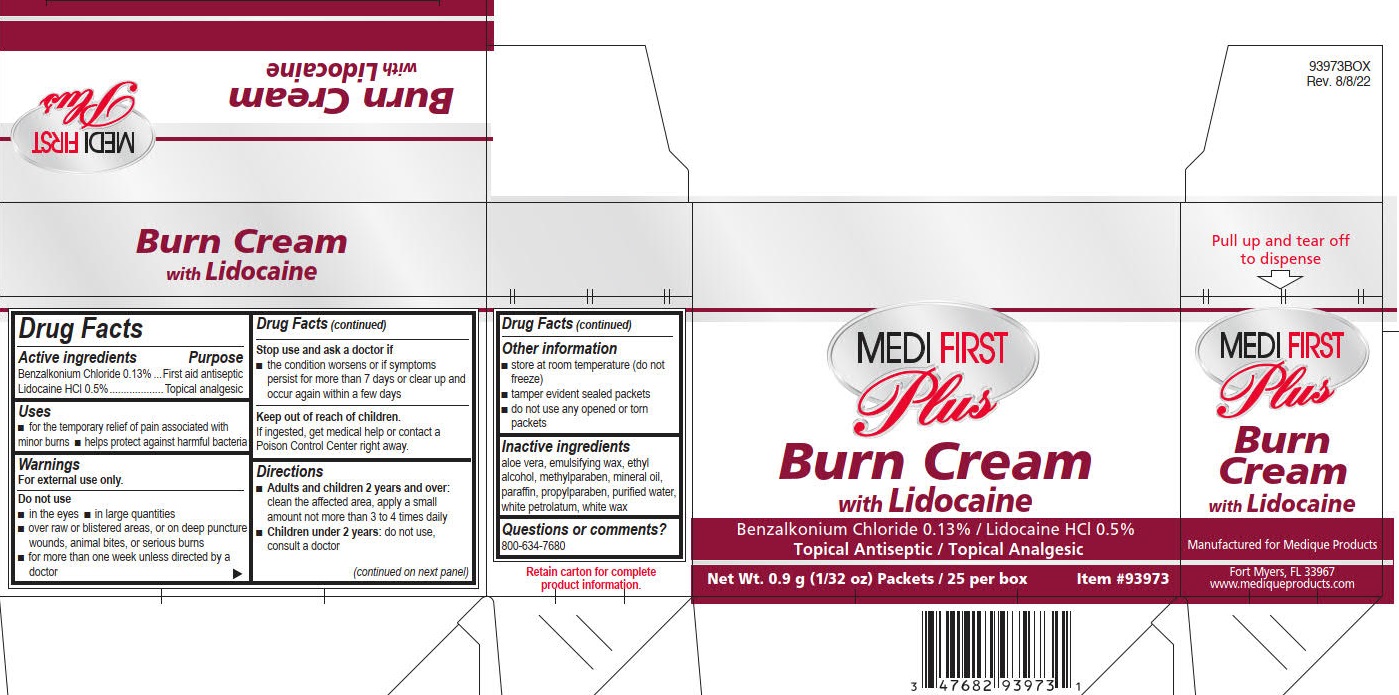 DRUG LABEL: Medi-First Plus Burn Cream
NDC: 47682-940 | Form: CREAM
Manufacturer: Unifirst First Aid Corporation
Category: otc | Type: HUMAN OTC DRUG LABEL
Date: 20250909

ACTIVE INGREDIENTS: LIDOCAINE HYDROCHLORIDE 5 mg/1 g; BENZALKONIUM CHLORIDE 1.3 mg/1 g
INACTIVE INGREDIENTS: ALOE VERA LEAF; ALCOHOL; METHYLPARABEN; MINERAL OIL; PARAFFIN; PETROLATUM; PROPYLPARABEN; WATER; WHITE WAX

Medi-First Plus Burn Cream

Drug Facts

Active ingredients

Benzalkonium Chloride 0.13%

Lidocaine HCl 0.5%

Purpose

First aid antiseptic

Topical analgesic

Uses

- for the temporary relief of pain associated with minor burns
- helps protect against harmful bacteria

Warnings

For external use only.

Do not use

- in the eyes
- in large quantities
- over raw or blistered areasover large areas, or on deep puncture wounds, animal bites, or serious burns
- for more than 1 week unless directed by a doctor

Stop use and ask a doctor if

- the condition gets worsens or if symptoms persist for more than 7 days or clear up and occur again within a few days

Keep out of reach of children.

Ifingested, get medical help or contact a Poison Control Center right away.

Directions

- Adults and children 12 years and over:

clean the affected area, apply a small amount not more than 3 to 4 times daily

- Children under 12 years:

do not use, consult a doctor

Other information

- store at room temperature (do not freeze)
- tamper evident sealed packets
- do not use any opened or torn packets

Inactive ingredients

aloe vera, emulsifying wax, ethyl alcohol, methylparaben, mineral oil, paraffin, propylparaben, purified water, white petrolatum, white wax

Questions or comments? 800-634-7680

Medi-First Plus Burn Cream Label

Medi First®

Plus

Burn Cream

with Lidocaine

Benzalkonium Chloride 0.13% / Lidocaine HCl 0.5%

Topical Antiseptic / Topical Analgesic

25 Units of 0.9g Packets

Item #93973